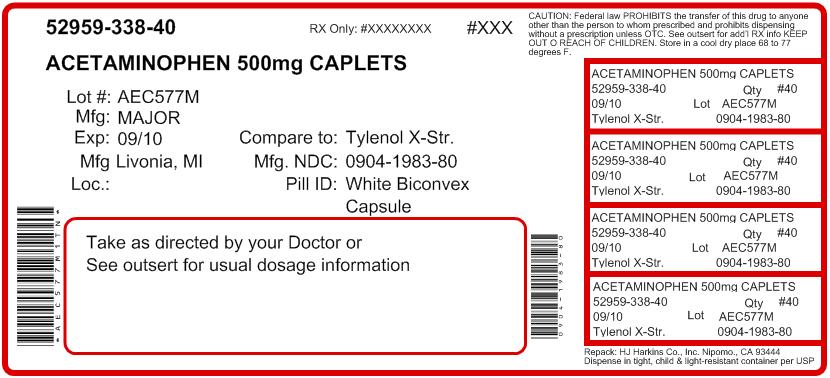 DRUG LABEL: Extra Strength Mapap
                        
NDC: 52959-338 | Form: TABLET, FILM COATED
Manufacturer: H.J. Harkins Company, Inc.
Category: otc | Type: HUMAN OTC DRUG LABEL
Date: 20120131

ACTIVE INGREDIENTS: ACETAMINOPHEN 500 mg/1 1
INACTIVE INGREDIENTS: HYPROMELLOSES; POLYETHYLENE GLYCOL; POVIDONE; STARCH, CORN; SODIUM STARCH GLYCOLATE TYPE A POTATO; STEARIC ACID

Drug Facts

Active Ingredient (in each caplet)

Acetaminophen 500 mg

Purpose

Pain Reliever/Fever Reducer

Uses

for the temporary relief of minor aches and pains due to:

- Headache
- Muscular aches
- Backache
- Minor pain of arthritis
- The common cold
- Toothache
- Premenstrual and menstrual cramps

Temporarily reduces fever.

Warnings

Liver warning: This product contains acetaminophen. Severe liver damage may occur if you take

- more than 8 caplets in 24 hours,which is the maximum daily amount
- with other drugs containing acetaminophen
- 3 or more alcoholic drinks every day while using this product

Do not use

- with any other drug containing acetaminophen (prescription or non prescription). If you are not sure whether a drug contains acetaminophen, ask a doctor or pharmacist.
- if you are allergic to acetaminophen or any of the inactive ingredients in this product

Ask a doctor before use if you have

liver disease

Ask a doctor or pharmacist before use if you are

taking the blood thinning drug warfarin

Stop use and ask a doctor if

- Pain gets worse or lasts more than 10 days
- Fever gets worse or lasts more than 3 days
- New symptoms occur
- Redness or swelling is present

These could be signs of a serious condition.

PREGNANCY OR BREAST FEEDING

If pregnant or breast-feeding, ask a health professional before use.

Keep out of reach of children

OVERDOSAGE

Overdose warning: Taking more than the recommended dose (overdose) may cause liver damage. In the case of overdose, get medical help or contact a Poison Control Center right away (1-800-222-1222). Quick medical attention is critical for adults as well as for children even if you do not notice any signs or symptoms.

Directions

Do not take more than directed

Adults and children 12 years and over:

- take 2 caplets every 4 to 6 hours while symptoms last
- do not take more than 8 caplets in 24 hours
- Do not take for more than 10 days unless directed by a doctor

Children under 12 years: do not use adult Extra Strength product in children under 12 years of age; this will provide more than the recommended dose (overdose) of acetaminophen and may cause liver damage.

Other information

- Do not use if imprinted safety seal under cap is broken or missing.
- store at room temperature

Inactive ingredients

Hypromellose, Polyethylene Glycol, Povidone, Pregelatinized Starch, Sodium Starch Glycolate, Stearic Acid

Questions?

Adverse Drug Events call (800) 616-2471

Repacked by:

H.J. Harkins Company, Inc.

513 Sandydale Drive

Nipomo, CA 93444

Principal Display Panel of Extra Strength Mapap 500 mg Caplets

NDC 0904-1983-60
MAJOR®

See New Warnings Information

Extra Strength
Mapap
ASPIRIN FREE
ACETAMINOPHEN
STRONG PAIN &
FEVER RELIEF
CAPLETS
Compare to active ingredient in Extra Strength Tylenol® Caplets*
*This product is not manufactured or distributed by McNeil Consumer Products Co., owner of the registered trademark Tylenol®.
100 Caplets
500 mg. Each
NDC 0904-1983-24
MAJOR®
EXTRA STRENGTH
Mapap

See New Warnings Information

ASPIRIN FREE
ACETAMINOPHEN
STRONG PAIN & FEVER RELIEF
CAPLETS
Compare to the active ingredients in Extra Strength Tylenol® Caplets*
See New Warning Information
24 Caplets
500 mg. Each
Repacked by:
H.J. Harkins Company, Inc.
Nipomo, CA 93444
*This product is not manufactured or distributed by McNeil Consumer Products Co., owner of registered trademark Tylenol®